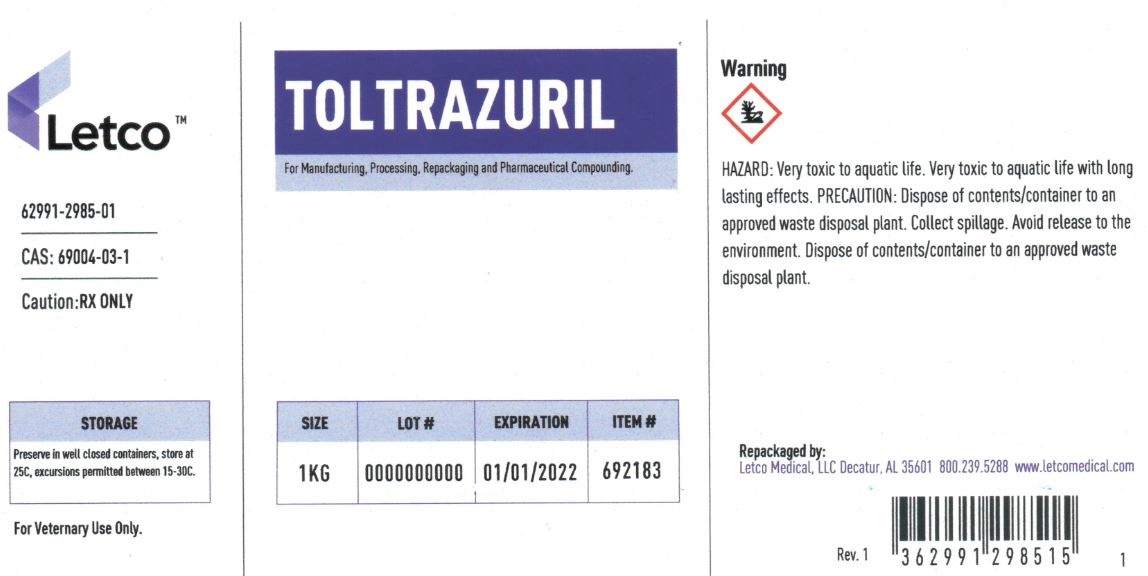 DRUG LABEL: Toltrazuril
NDC: 62991-2985 | Form: POWDER
Manufacturer: LETCO MEDICAL, LLC
Category: other | Type: BULK INGREDIENT - ANIMAL DRUG
Date: 20240718

ACTIVE INGREDIENTS: TOLTRAZURIL 1 kg/1 kg

Toltrazuril

PACKAGE LABEL

Toltrazuril 1kg